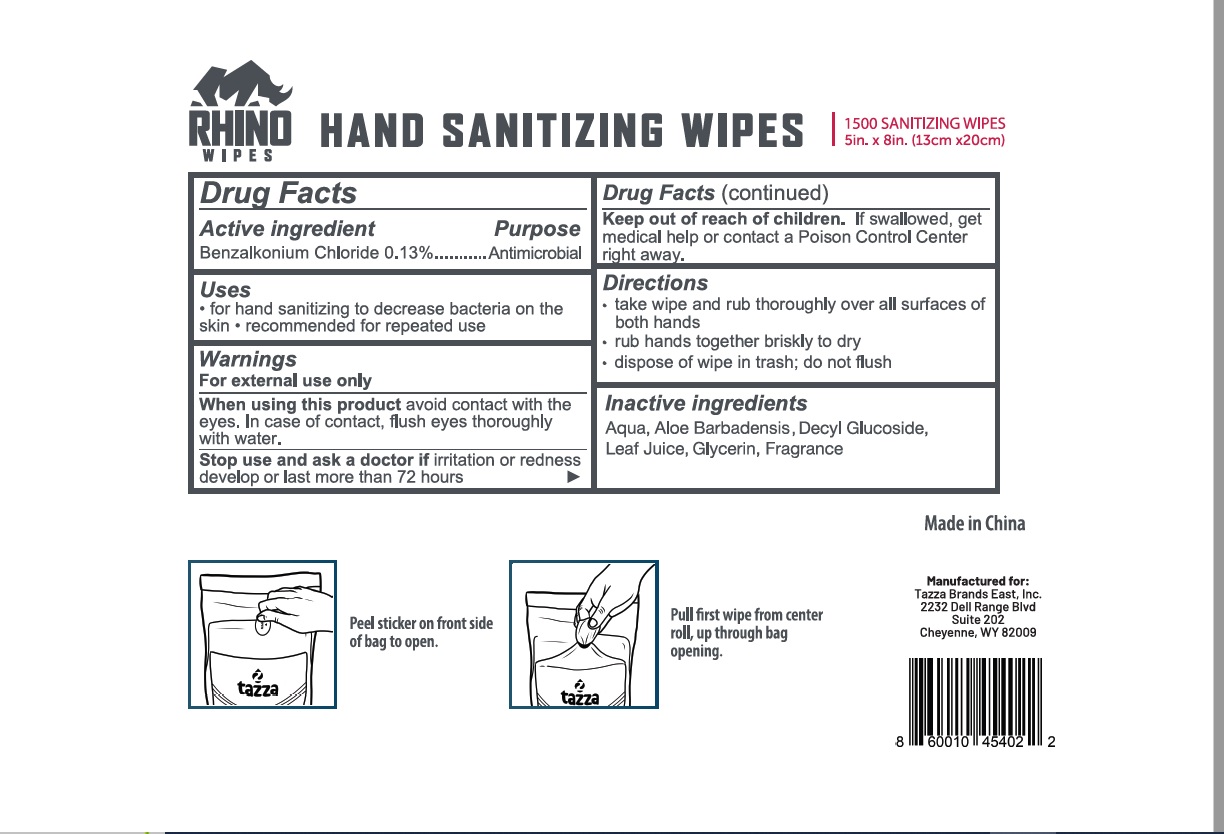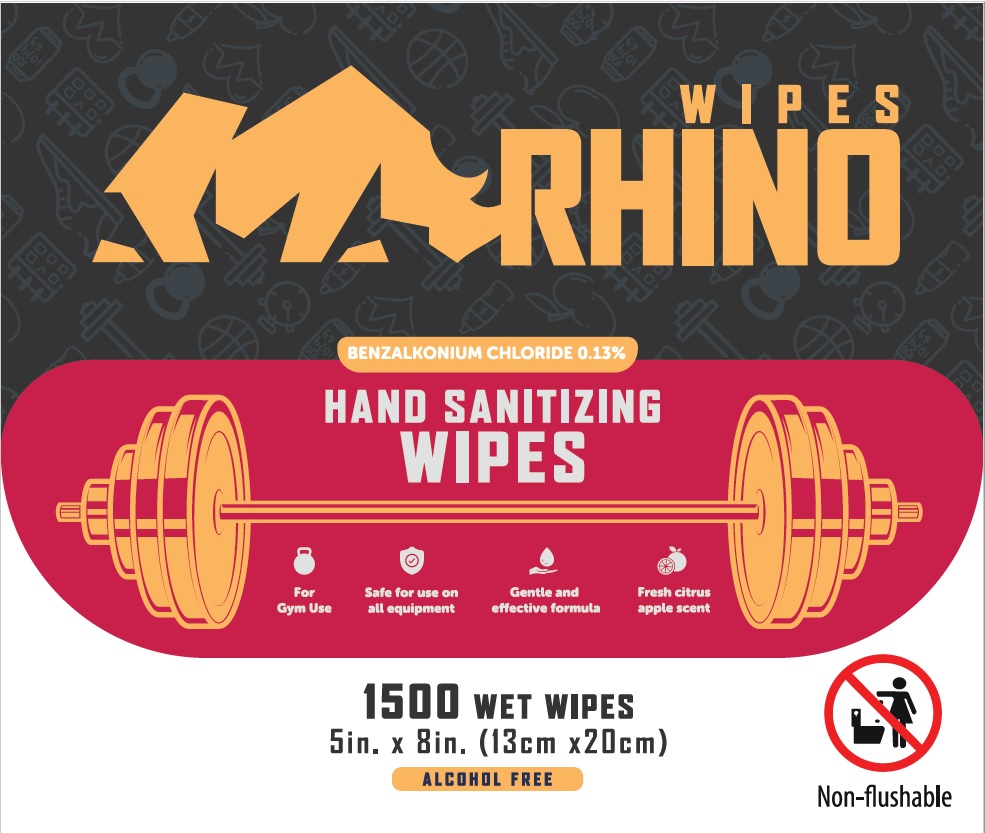 DRUG LABEL: RHINO Hand Sanitizing Wipes
NDC: 76370-0026 | Form: CLOTH
Manufacturer: Tazza Brands East, Inc.
Category: otc | Type: HUMAN OTC DRUG LABEL
Date: 20240723

ACTIVE INGREDIENTS: BENZALKONIUM CHLORIDE 0.13 g/100 mL
INACTIVE INGREDIENTS: GLYCERIN; ALOE VERA LEAF; DECYL GLUCOSIDE; WATER

Rhino Wipes

Drug Facts

Active ingredient

Benzalkonium chloride 0.13%

Purpose

Antimicrobial

Uses

- for hand sanitizing to decrease bacteria on the skin
- recommended for repeated use

Warnings

For external use only

When using this product avoid contact with the eyes. In case of contact, flush eyes thoroughly with water.

Stop use and ask a doctor if irritation or redness develop or last more than 72 hours.

Keep out of reach of children. If swallowed, get medical help or contact a Poison Control Center right away.

Directions

- take wipe and rub thoroughly over all surfaces of both hands
- rub hands together briskly to dry
- dispose of wipe in trash; do not fliush

INACTIVE INGREDIENT

Inactive ingredients Aqua, Aloe Barbadensis Leaf Juice, Decyl Glucoside, Glycerin, Fragrance

Made in China

Manufactured for:

Tazza Brands East, Inc.

2232 Dell Range Blvd

Suite 202

Cheyenne, WY 82009

PACKAGE LABEL

RHINO WIPES

Benzalkonium Chloride 0.13%

HAND SANITIZING WIPES

1500 Wet Wipes

5 in. x 8 in. (13cm x 20cm)

Alcohol Free